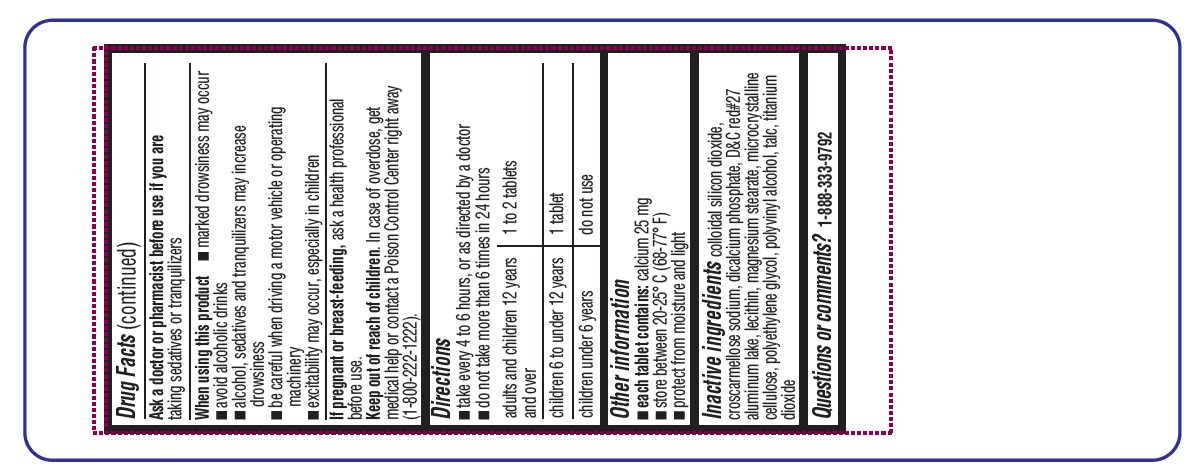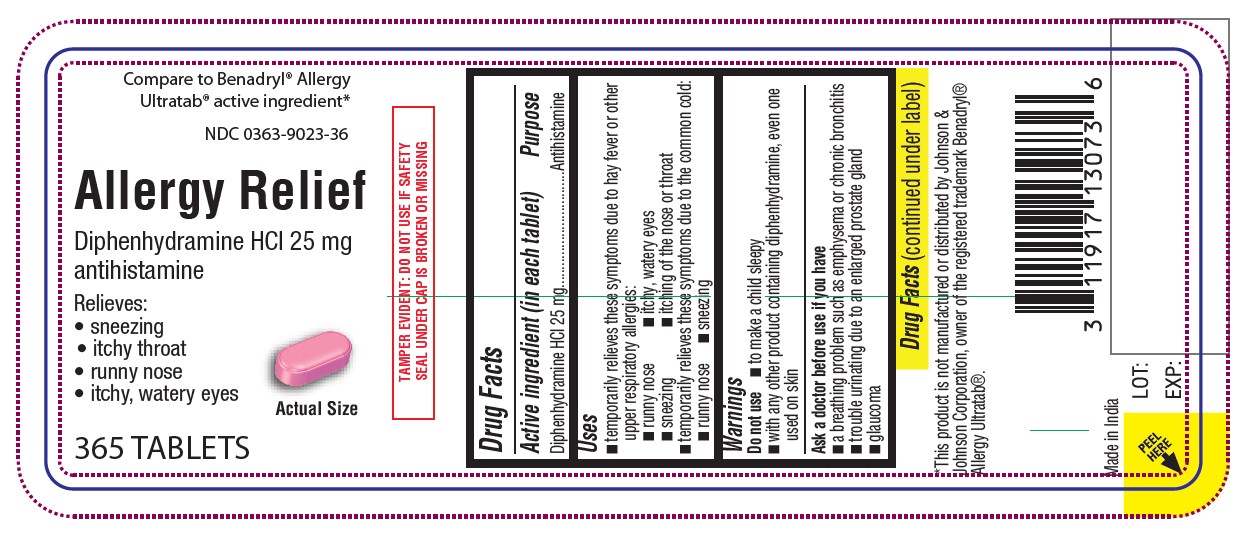 DRUG LABEL: Allergy Relief
NDC: 0363-9023 | Form: TABLET, FILM COATED
Manufacturer: Walgreens
Category: otc | Type: HUMAN OTC DRUG LABEL
Date: 20260119

ACTIVE INGREDIENTS: DIPHENHYDRAMINE HYDROCHLORIDE 25 mg/1 1
INACTIVE INGREDIENTS: SILICON DIOXIDE; CROSCARMELLOSE SODIUM; CALCIUM PHOSPHATE; D&C RED NO. 27; LECITHIN, SOYBEAN; MAGNESIUM STEARATE; MICROCRYSTALLINE CELLULOSE; POLYETHYLENE GLYCOL, UNSPECIFIED; POLYVINYL ALCOHOL, UNSPECIFIED; TALC; TITANIUM DIOXIDE

Allergy Relief

Active ingredient (in each tablet)

Diphenhydramine HCl 25 mg

Purpose

Antihistamine

Uses

• temporarily relieves these symptoms due to hay fever or other upper respiratory allergies:
• runny nose
• itchy, watery eyes
• sneezing
• itching of the nose or throat
• temporarily relieves these symptoms due to the common cold:
• runny nose
• sneezing

Warnings

Do not use

• to make a child sleepy
• with any other product containing diphenhydramine, even one used on skin

Do not use

• to make a child sleepy
• with any other product containing diphenhydramine, even one used on skin

Ask a doctor or pharmacist before use if you are taking sedatives or tranquilizers

When using this product

• marked drowsiness may occur
• avoid alcoholic drinks
• alcohol, sedatives and tranquilizers may increase drowsiness
• be careful when driving a motor vehicle or operating machinery
• excitability may occur, especially in children

PREGNANCY OR BREAST FEEDING

If pregnant or breast-feeding, ask a health professional before use.

Keep out of reach of children. In case of overdose, get medical help or contact a Poison Control Center right away.

Directions

- take every 4 to 6 hours
- do not take more than 6 doses in 24 hours

adults and children 12 years of age and over | 1 to 2 tablets
children 6 to under 12 years of age | 1 tablet
children under 6 years of age | do not use this product in children under 6 years of age

Other information

- store at controlled room temperature 15°-30° C (59°-86° F)
- protect from moisture and light
- see end flap for expiration date and lot number
- each tablet contains calcium 24 mg

Inactive ingredients

colloidal silicon dioxide, croscarmellose sodium, dicalcium phosphate, D&C red # 27 Al lake, lecithin, magnesium stearate, microcrystalline cellulose, polyethylene glycol, polyvinyl alcohol, talc, titanium dioxide

Questions or comments?

1-888-333-9792